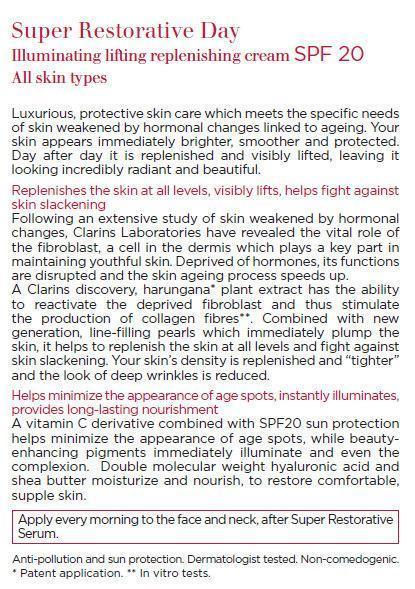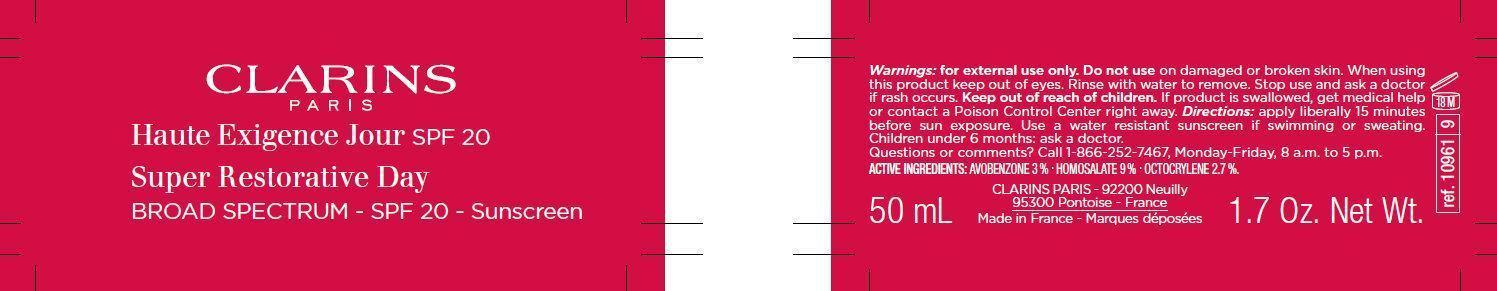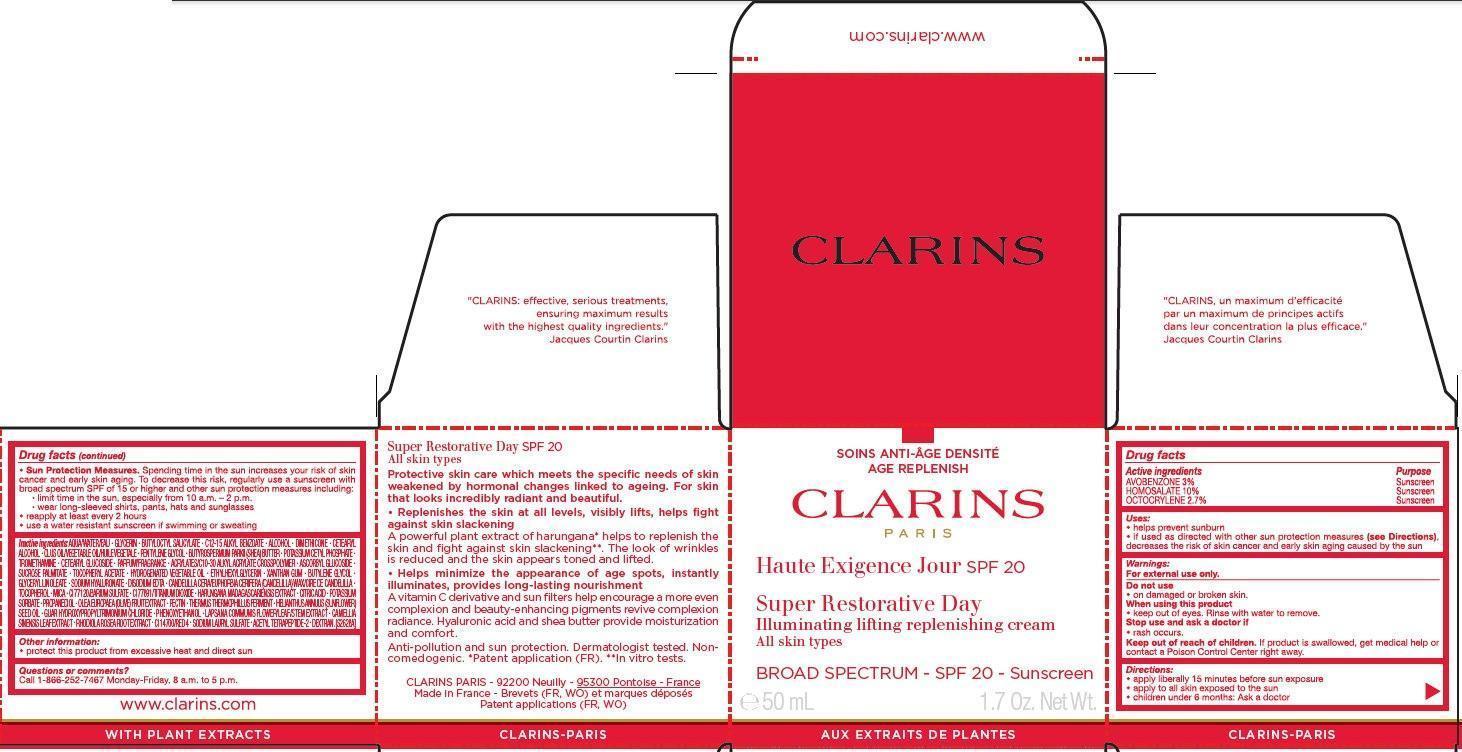 DRUG LABEL: CLARINS Super Restorative Day Illuminating lifting replenishing BROAD SPECTRUM - SPF 20 - Sunscreen
NDC: 58668-0961 | Form: CREAM
Manufacturer: Laboratoires Clarins
Category: otc | Type: HUMAN OTC DRUG LABEL
Date: 20241231

ACTIVE INGREDIENTS: AVOBENZONE 30 mg/1 mL; HOMOSALATE 100 mg/1 mL; OCTOCRYLENE 27 mg/1 mL
INACTIVE INGREDIENTS: WATER; GLYCERIN; BUTYLOCTYL SALICYLATE; ALKYL (C12-15) BENZOATE; ALCOHOL; DIMETHICONE; CETOSTEARYL ALCOHOL; PENTYLENE GLYCOL; SHEA BUTTER; POTASSIUM CETYL PHOSPHATE; TROMETHAMINE; CETEARYL GLUCOSIDE; ASCORBYL GLUCOSIDE; SUCROSE PALMITATE; .ALPHA.-TOCOPHEROL ACETATE; ETHYLHEXYLGLYCERIN; XANTHAN GUM; BUTYLENE GLYCOL; GLYCERYL MONOLINOLEATE; HYALURONATE SODIUM; EDETATE DISODIUM; CANDELILLA WAX; TOCOPHEROL; MICA; BARIUM SULFATE; TITANIUM DIOXIDE; CITRIC ACID MONOHYDRATE; POTASSIUM SORBATE; PROPANEDIOL; BLACK OLIVE; PECTIN; THERMUS THERMOPHILUS LYSATE; SUNFLOWER OIL; PHENOXYETHANOL; LAPSANA COMMUNIS FLOWERING TOP; GREEN TEA LEAF; SEDUM ROSEUM ROOT; FD&C RED NO. 4; SODIUM LAURYL SULFATE

CLARINS Super Restorative Day Illuminating lifting replenishing cream BROAD SPECTRUM - SPF 20 - Sunscreen

Active ingredients

AVOBENZONE 3% HOMOSALATE 10% OCTOCRYLENE 2.7%

Purpose

Sunscreen

Uses:

- helps prevent sunburn
- if used as directed with other sun protection measures decreases the risk of skin cancer and early skin aging caused by the sun (see Directions),

Warnings:

For external use only.

Do not use

- on damaged or broken skin.

When using this product

- keep out of eyes. Rinse with water to remove.

Stop use and ask a doctor if

- rash occurs.

Keep out of reach of children.

If product is swallowed, get medical help or contact a Poison Control Center right away.

Directions:

- apply liberally 15 minutes before sun exposure
- apply to all skin exposed to the sun
- children under 6 month: Ask a doctor
- Spending time in the sun increases your risk of skin cancer and early skin aging. To decrease the risk, regularly use a sunscreen with broad spectrum SPF of 15 or higher and other sun protection measures including: Sun Protection Measures.
- limit time in the sun, especially from 10 a.m. - 2 p.m.
- wear long-sleeved shirts, pants, hats and sunglasses
- reapply at least every 2 hours
- use a water resistant sunscreen if swimming or sweating

Inactive ingredients:

AQUA/WATER/EAU - GLYCERIN - BUTYLOCTYL SALICYLATE - C12-15 ALKYL BENZOATE - ALCOHOL - DIMETHICONE - CETEARYL ALCOHOL - OLUS OIL/VEGETABLE OIL/HUILE VEGETALE - PENTYLENE GLYCOL - BUTYROSPERMUM PARKII (SHEA) BUTTER - POTASSIUM CETYL PHOSPHATE - TROMETHAMINE - CETEARYL GLUCOSIDE - PARFUM/FRAGRANCE - ACRYLATES/C10-30 ALKYL ACRYLATE CROSSPOLYMER - ASCORBYL GLUCOSIDE - SUCROSE PALMITATE - TOCOPHERYL ACETATE - HYDROGENATED VEGETABLE OIL - ETHYLHEXYLGLYCERIN - XANTHAN GUM - BUTYLENE GLYCOL - GLYCERYL LINOLEATE - SODIUM HYALURONATE - DISODIUM EDTA - CANDELILLA CERA/EUPHORBIA CERIFERA (CANDELILLA) WAX/CIRE DE CANDELILLA - TOCOPHEROL - MICA - CI 77120/BARIUM SULFATE - CI 77891/TITANIUM DIOXIDE - HARUNGANA MADAGASCARIENSIS EXTRACT - CITRIC ACID - POTASSIUM SORBATE - PROPANEDIOL - OLEA EUROPAEA (OLIVE) FRUIT EXTRACT - PECTIN - THERMUS THERMOPHILUS FERMENT - HELIANTHUS ANNUUS (SUNFLOWER) SEED OIL - GUAR HYDROXYPROPYLTRIMONIUM CHLORIDE - PHENOXYETHANOL - LAPSANA COMMUNIS FLOWER/LEAF/STEM EXTRACT - CAMELLIA SINENSIS LEAF EXTRACT - RHODIOLA ROSEA ROOT EXTRACT - CI 14700/RED 4 - SODIUM LAURYL SULFATE - ACETYL TETRAPEPTIDE-2 - DEXTRAN. [S2628A]

Other information:

- protect this product from excessive heat and direct sun

Questions or comments?

Call 1-866-252-7467 Monday-Friday, 8 a.m. to 5 p.m.

"CLARINS: effective, serious treatments, ensuring maximum results with the highest quality ingredients." Jacques Courtin Clarins

Super Restorative Day SPF 20 All skin types Protective skin care which meets the specific needs of skin weakened by hormonal changes linked to ageing. For skin that looks incredibly radiant and beautiful. • Replenishes the skin at all levels, visibly lifts, helps fight against skin slackening A powerful plant extract of harungana* helps to replenish the skin and fight against skin slackening**. The look of wrinkles is reduced and the skin appears toned and lifted. • Helps minimize the appearance of age spots, instantly illuminates, provides long-lasting nourishment A vitamin C derivative and sun filters help encourage a more even complexion and beauty-enhancing pigments revive complexion radiance. Hyaluronic acid and shea butter provide moisturization and comfort. Anti-pollution and sun protection. Dermatologist tested. Noncomedogenic. *Patent application (FR). **In vitro tests.

CLARINS PARIS - 92200 Neuilly - 95300 Pontoise - France Made in France - Brevets (FR, WO) et marques déposés Patent applications (FR, WO) www.clarins.com CLARINS-PARIS

18 M ref. 10961 9

PACKAGE LABEL

CLARINS PARIS

Haute Exigence Jour SPF 20

Super Restorative Day Illuminating lifting replenishing cream All skin types

BROAD SPECTRUM - SPF 20 - Sunscreen

e 50 mL 1.7 Oz. Net Wt.